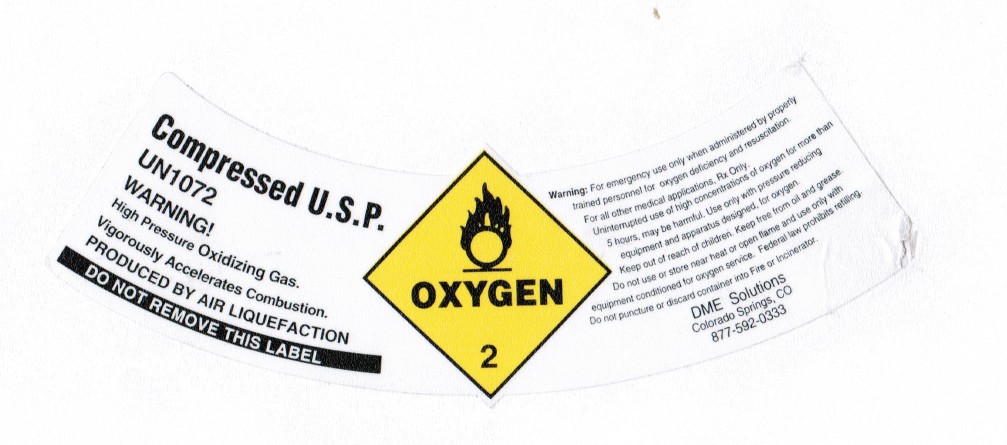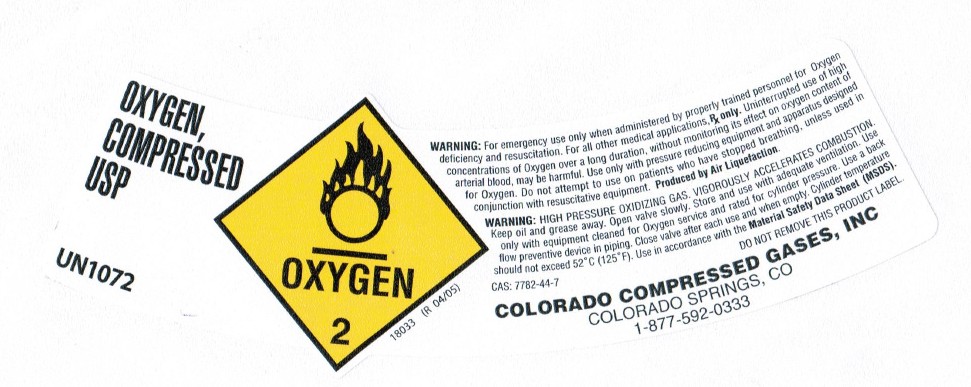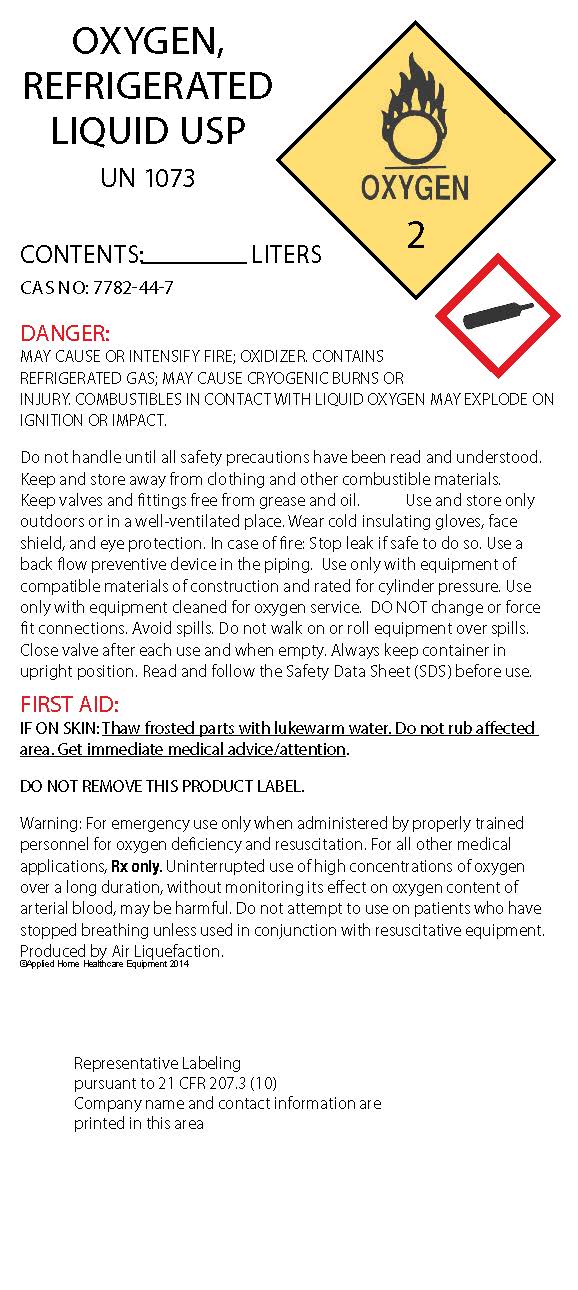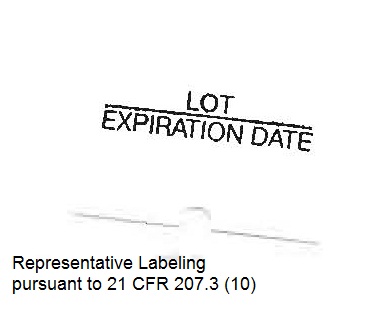 DRUG LABEL: Oxygen
NDC: 68769-002 | Form: GAS
Manufacturer: Colorado Compressed Gases
Category: prescription | Type: HUMAN PRESCRIPTION DRUG LABEL
Date: 20231128

ACTIVE INGREDIENTS: OXYGEN 99 L/100 L

Oxygen

Principal for Oxygen Product

Compressed U.S.P

UN1072

WARNING!

High Pressure Oxidizing Gas.

Vigorously Accelerates Combustion.

PRODUCED BY AIR LIQUEFICATION

DO NOT REMOVE THIS LABEL

Warning: For emergency use only when administered by properly

trained personnel for oxygen deficiency and resuscitation.

For all other medical applications. Rx Only.

Uinterrupted use of high concentrations of oxygen for more than

5 hours may be harmful. Use only with pressure reducing

equipment and apparatus designed for oxygen.

Keep out of reach of children. Keep free from oil and grease.

Do not use or store near heat or open flame and use only with

equipment conditioned for oxygen service. Federal law prohibits refilling.

Do not puncture or discard container into Fire of Incinerator.

OXYGEN

COMPRESSED

USP

UN1072

WARNING: For emergency use only when administered by properly trained personnel for Oxygen deficiency and resuscitation. For all other medical applications. Rx only. Uninterrupted use of high concentrations of Oxygen over a long duration, without monitoring its effect on oxygen content of arterial blood may be harmful. Use only with pressure reducing equipment and apparatus designed for Oxygen. Do not attempt to use on patients who have stopped breathing unless used in conjunction with resuscitative equipment. Produced by Air Liquefication.

WARNING: HIGH PRESSURE OXIDIZING GAS. VIGOROUSLY ACCELERATES COMBUSTION. Keep oil and grease away. Open valve slowly. Store and use with adequate ventilation. Use only with equipment cleaned for Oxygen service and rated for cylinder pressure. Use a back flow preventive device in piping. Close valve after each use when empty. Cylinder temperature should not exceed 52 °C (125 °F). Use in accordance with the Material Safety Data Sheet (MSDS).

CAS 7762-44-7

OXYGEN,

REFRIGERATED

LIQUID USP

UN 1073

CONTENTS ________________LITERS

CAS NO: 7782-44-7

DANGER:

MAY CAUSE OR INTENSIFY FIRE; OXIDIZER. CONTAINS

REFRIGERATED GAS; MAY CAUSE CRYOGENIC BURNS OR

INJURY. COMBUSTIBLES IN CONTACT WITH LIQUID OXYGEN MAY EXPLODE ON

IGNITION OR IMPACT.

Do not handle until all safety precautions have been read and understood.

Keep and store away from clothing and other combustible materials.

Keep valves and fittings free from grease and oil. Use and store only

outdoors or in a well-ventilated place. Wear cold insulating gloves, face

shield, and eye protection. In case of fire: Stop leak if safe to do so. Use a

back flow preventive device in the piping. Use only with equipment of

compatible materials of construction and rated for cylinder pressure. Use

only with equipment cleaned for oxygen service. DO NOT change or force

fit connections. Avoid spills. Do not walk on or roll equipment over spills.

Close valve after each use and when empty. Always keep container in

upright position. Read and follow the Safety Data Sheet (SDS) before use.

FIRST AID:

IF ON SKIN: Thaw frosted parts with lukewarm water. Do not rub affected

area. Get immediate medical advice/attention.

DO NOT REMOVE THIS PRODUCT LABEL.

Warning: For emergency use only when administered by properly trained

personnel for oxygen deficiency and resuscitation. For all other medical

applications, Rx only. Uninterrupted use of high concentrations of oxygen

over a long duration, without monitoring its effect on oxygen content of

arterial blood, may be harmful. Do not attempt to use on patients who have

stopped breathing unless used in conjunction with resuscitative equipment.

Produced by Air Liquefaction.